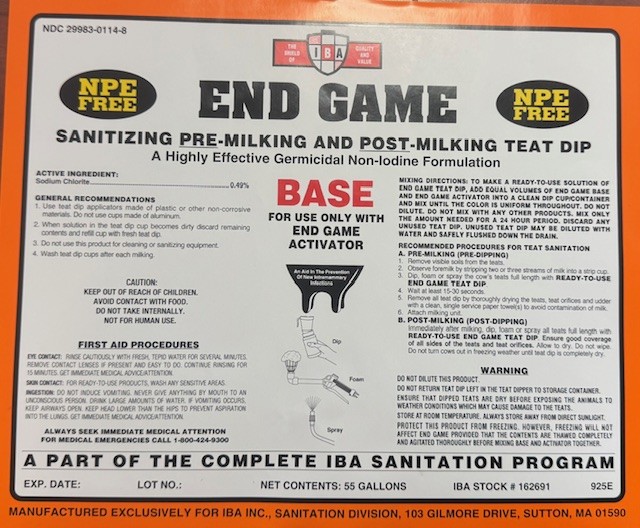 DRUG LABEL: END GAME BASE
NDC: 29983-0114 | Form: SOLUTION
Manufacturer: IBA
Category: animal | Type: OTC ANIMAL DRUG LABEL
Date: 20251001

ACTIVE INGREDIENTS: SODIUM CHLORITE 0.49 g/1 L

END GAME SANITIZING PRE-MILING AND POST MILKING TEAT DIP A HIGHLY EFFECTIVE GERMICIDAL NON-IODINE FORMULATION

ACTIVE INGREDIENT

SODIUM CHLORITE...........0.49%

INDICATIONS AND USAGE

GENRAL RECOMMENDATIONS

1. Use teat dip applicators made of plastic or other non-corrosive materials. Do not use cups made of aluminum.
2. When solution in the teat dip cup becomes dirty and/or noticeably loses color, discard remaining contents and refill cup with fresh teat dip.
3. Do not use this product for cleaning or sanitizing equipment
4. Wash Teat Dip cups after each milking.

MIXING DIRECTIONS: TO MAKE A READY-TO-USE SOLUTION OF END GAME TEAT DIP, ADD EQUAL VOLUMES OF END GAME BASE AND END GAME ACTIVATOR INTO A CLEAN DIP CUP/CONTAINER AND MIX UNTIL THE COLOR IS UNIFORAM THROUGHOUT. DO NOT DILUET. DO NOT MIX WITH ANY OTHER PRODUCTS. MIX ONLY THE AMOUNT NEEDED FOR A 24 HR PERIOD. DISCARD ANY UNUSED TEAT DIP. UNUSED TEAT DIP MAY BE DILUTED WITH WATER AND SAFELY FLUSHED DOWN THE DRAIN.

RECOMMENDED PROCEDURES FOR TEAT SANITATION

A. PRE-MILKING (PRE-DIPPING)

1. Remove visible soils from the teats.

2. Observe foremilk by strippping two or three streams of milk into a strip cup.

3. Dip or Spray the cow's teats full lenth with READY-TO-USE END GAME TEAT DIP.

4. Waut at least 15-30 seconds

5. Remove all teat dip by thoroughly drying the teats, teat orifices and udder with a clean, single service paper towel(s) to avoid contamination of milk.

6, Attach milking unit
POST-MILKING (POST DIPPING)

Immediately after milking, dip or spray all teats full length with READY-TO-USE END GAME TEAT DIP. Ensure good coverage of all sides of the teats and teat orifices. Allow to dry. Do not wipe. Do not turn cows out in freezing weather until teat dip is completely dry.

WARNING

DO NOT DILUTE THIS PRODUCT
DO NOT RETURN TEAT DIP LEFT IN THE TEAT DIPPER TO STORAGE CONTAINER
ENSURE THAT DIPPED TEATS ARE DRY BEFORE EXPOSING THE ANIMALS TO WEATHER CONDITIONS WHICH MAY CAUSE DAMAGE TO THE TEATS.

STORE AT ROOM TEPERATURE. ALWAYS STORE AWAY FROM DIRECT SUNLIGHT.

PROTECT THIS PRODUCT FROM FREEZING. HOWEVER, FREEZING WILL NOT AFFECT END GAME PROVIDED THAT THE CONTENTS ARE THAWED COMPLETELY AND AGITATED THOROUGHLY BEFORE MIXING BASE AND ACTIVATOR TOGETHER.

CAUTION: KEEP OUT OF REACH OF CHILDREN.
AVOID CONTACT WITH FOOD. DO NOT TAKE INTERNALLY.

FIRST AID PROCEDURES

EYE CONTACT: ARINSE CAUSTIOUSLY WITH FRESH,TEPID WATER FOR SEVERAL MINUTES.REMOVE CONTACT LENSES IF PRESENT AND EASY TO DO. CONTINUE RINSING FOR 15 MINUTES. GET IMMEDIATE MEDICAL ADVICE/ATTENTION.

SKIN CONTACT: FOR READY-TO-USE PRODUCTS, WASH ANY SENSITIVE AREAS.

INGESTION: DO NOT INDUCE VOMITING.NEVER GIVE ANYTHING BY MOUTH TO AN UNCONSCIOUS PERSON.DRINK LARGE AMOUNTS OF WATER. IF VOMITING OCCURS, KEEP AIRWAYS OPEN. KEEP HEAD LAWER THAN THE HIPS TO PREVENT ASPIRATION INTO THE LUNGS. GET IMMEDIATE MEDICAL ADVISE/ATTENTION.

ALWAYS SEEK IMMEDIATE MEDICAL ATTENTION

FOR MEDICAL EMERGENCIES CALL 1-800-424-9300